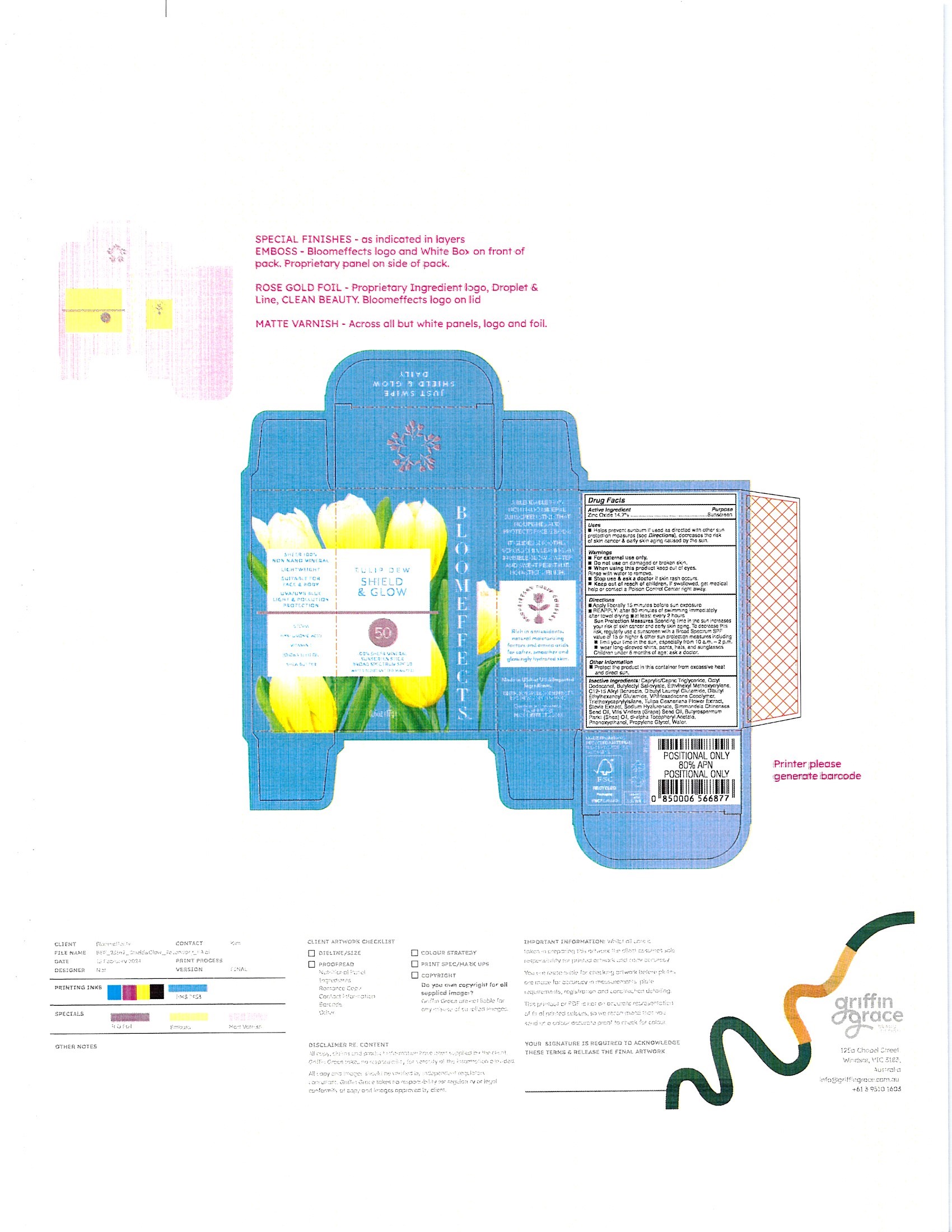 DRUG LABEL: Tulip Dew SHIELD GLOW
NDC: 82548-2420 | Form: STICK
Manufacturer: Bloomeffects, Inc.
Category: otc | Type: HUMAN OTC DRUG LABEL
Date: 20250723

ACTIVE INGREDIENTS: ZINC OXIDE 14.7 g/100 g
INACTIVE INGREDIENTS: .ALPHA.-TOCOPHEROL ACETATE, DL-; SHEANUT OIL; MEDIUM-CHAIN TRIGLYCERIDES; BUTYLOCTYL SALICYLATE; DIBUTYL LAUROYL GLUTAMIDE; DIBUTYL ETHYLHEXANOYL GLUTAMIDE; PHENOXYETHANOL; PROPYLENE GLYCOL; STEVIA REBAUDIUNA LEAF; TRIETHOXYCAPRYLYLSILANE; ETHYLHEXYL METHOXYCRYLENE; JOJOBA OIL; VINYLPYRROLIDONE/HEXADECENE COPOLYMER; WATER; 2-HEXYLDODECANOL; ALKYL (C12-15) BENZOATE; HYALURONATE SODIUM; GRAPE SEED OIL; MAGNOLIA LILIIFLORA FLOWER BUD

Tulip Dew SHIELD GLOW 100 Sheer Mineral Sunscreen Stick Broad Spectrum SPF 50 (IS0382-BF)

Active Ingredients

Zinc Oxide 14.7%

When using this product keep out of eyes. Rinse with water to remove.

WARNINGS

For external use only.

Stop use & ask a doctor if skin eash occurs.

Keep out of reach of children. If swallowed, get medical help or contact a Poison Control Center righ away.

Do not use on damaged or broken skin.

Inactive Ingredients

Caprylic/Capric Triglyceride
Butyloctyl Salicylate
Butyrospermum Parkii(Shea) Oil
C12-15 Alkyl Benzoate
Dibutyl Ethylhexanoyl Glutamide
Dibutyl Lauroyl Glutamide
dl-alpha Tocopheryl Acetate
Ethylhexyl Methoxycrylene
Octyl Dodecanol
Phenoxyethanol
Propylene glycol
Simmondsia Chinenses Seed oil
Stevia Extract
Sodium hyaluronate
Triethoxycaprylylsilane
Tulipa Gesneriana Flower Extract
Vitis Vinifera (Grape) Seed Oil
VP/Hexadecene Copolymer
Water

PURPOSE

Sunscreen